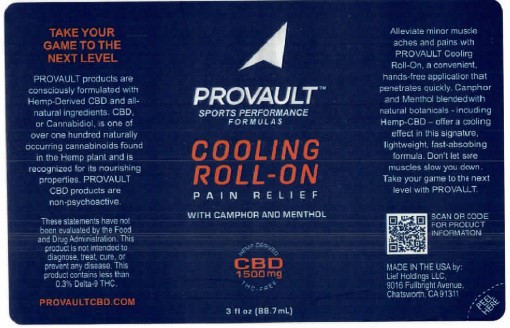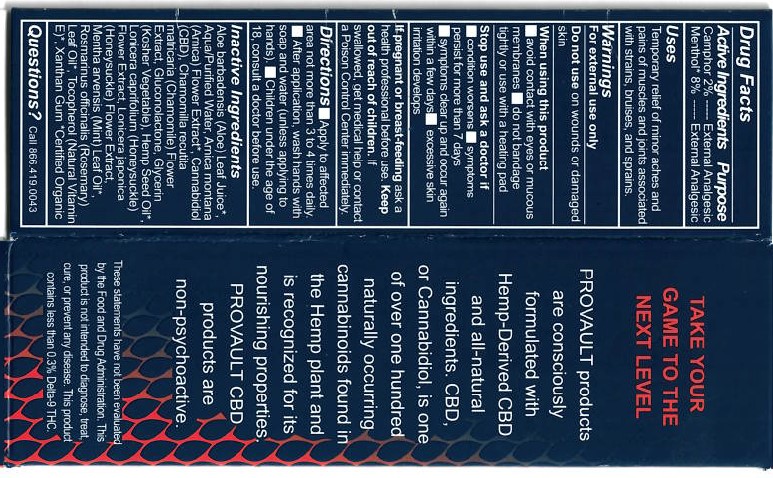 DRUG LABEL: Provault Cooling Roll on
NDC: 61577-6100 | Form: GEL
Manufacturer: Sombra Cosmetics Inc
Category: otc | Type: HUMAN OTC DRUG LABEL
Date: 20221019

ACTIVE INGREDIENTS: MENTHOL .08 g/1 g; CAMPHOR (NATURAL) .02 g/1 g
INACTIVE INGREDIENTS: WATER; CANNABIDIOL; TOCOPHEROL; ALOE VERA LEAF; GLUCONOLACTONE; glycerin; XANTHAN GUM; ARNICA MONTANA FLOWER WATER; ROSEMARY OIL; CHAMOMILE; HEMP; LONICERA JAPONICA FLOWER; MENTHA ARVENSIS FLOWER OIL

Provault Cooling Roll on

Active Ingredients

Menthol USP 8%, Camphor USP 2%

Purpose

External Analgesic

Keep out of reach of children

Uses

Temporary relief of monor aches and pains of muscles and joints associated with strains, bruises and sprains.

Warnings

For external use only.

Directions

Apply to affected area not more than 3 to 4 times daily. After each application, wash hands with soap and water (unless applying to hands). Children under the age of 18, consult a doctor before use.

Inactive Ingredients

Aloe Baradensis (Aloe) Leaf Juice, Aqua/Purified Water, Arnica Montana (Arnica) Flower Extract, Cannabidiol (CBD), Chamomilla Recutita (Chamomile) Flower Extract, Gluconolactone, Glycerin (Kosher Vegetable), Hemp Seed Oil, Lonicera Japonica (Honeysuckle) Flower Extract, Mentha Arvensis (mint) Leaf Oil, Rosmarinus Officinalis (Rosemary) Leaf Oil, Tocopherol (Natural Vitamin E), Xanthan Gum.

Questions or Comments

Call 866 419 0043